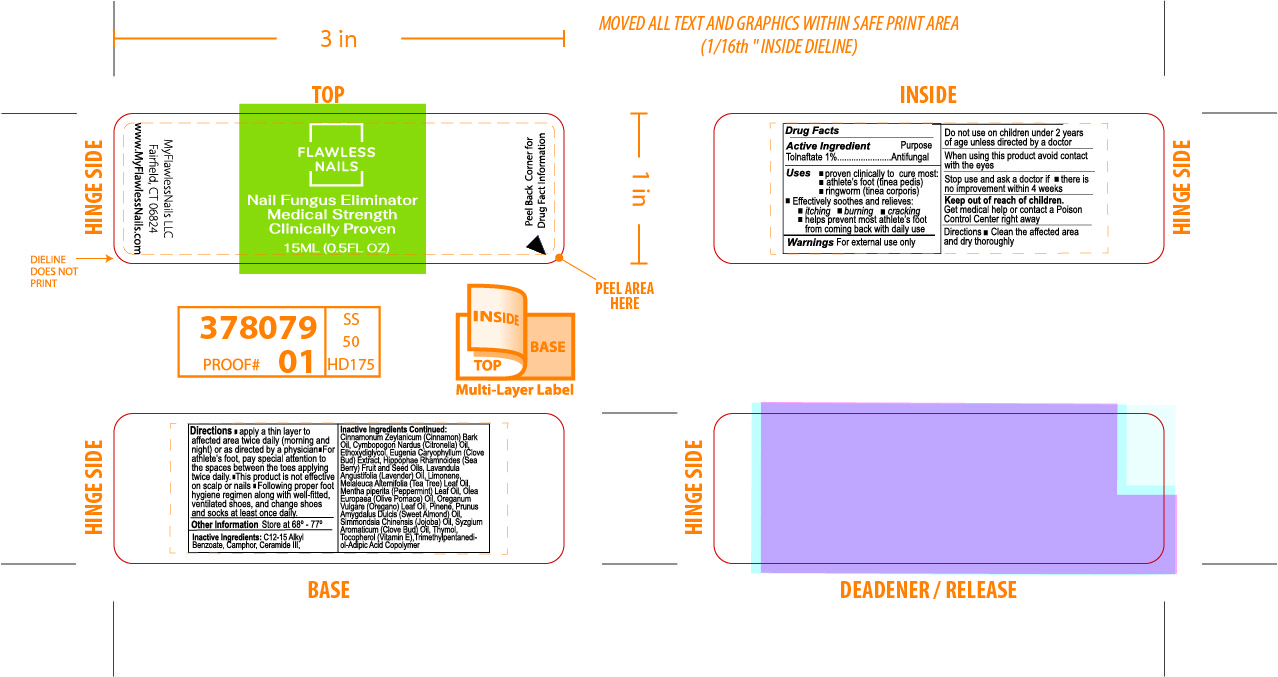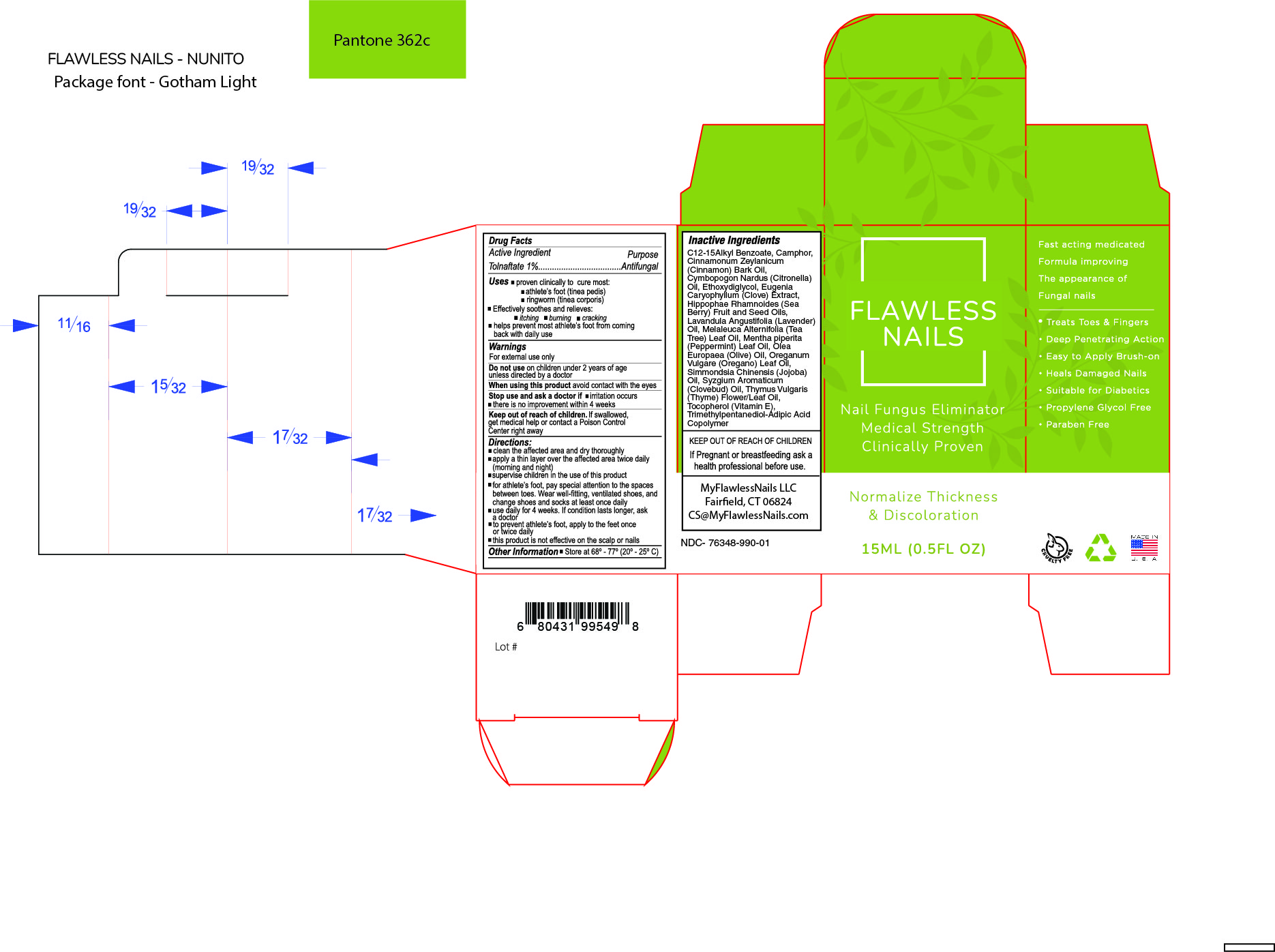 DRUG LABEL: FLAWLESS NAILS
NDC: 76348-990 | Form: SOLUTION
Manufacturer: RENU LABORATORIES, INC.
Category: otc | Type: HUMAN OTC DRUG LABEL
Date: 20230105

ACTIVE INGREDIENTS: TOLNAFTATE 1 g/100 mL
INACTIVE INGREDIENTS: CAMPHOR (NATURAL); CINNAMON BARK OIL; HIPPOPHAE RHAMNOIDES FRUIT OIL; TRIMETHYLPENTANEDIOL/ADIPIC ACID/GLYCERIN CROSSPOLYMER (25000 MPA.S); PINENE; ALMOND OIL; PEPPERMINT OIL; .ALPHA.-TOCOPHEROL ACETATE; CLOVE; LAVENDER OIL; LIMONENE, (+)-; ALKYL (C12-15) BENZOATE; TEA TREE OIL; HIPPOPHAE RHAMNOIDES SEED OIL; DIETHYLENE GLYCOL MONOETHYL ETHER; CITRONELLA OIL; CERAMIDE 3; OLIVE OIL; OREGANO LEAF OIL; JOJOBA OIL; CLOVE OIL; THYMOL

Flawless Nails

ACTIVE INGREDIENT

Tolnaftate

QUESTIONS

MyFlawlessNails LLC

Fairfield, CT 06824

www.MyFlawlessNails.com

STATEMENT OF IDENTITY

FLAWLESS NAILS

Nail Fungus Eliminator

Medical Strength

Clinically Proven

15ML (O.5FL.OZ)

RECENT MAJOR CHANGES

No major changes in Directions. We forgot to save the section and had to retype it.

Only changes made in Dosage were the removal of bullets and unapproved punctuation.

Other information: Store at 68° - 77°

Inactive Ingredients

C12-15 Alkyl Benzoate, Camphor, Ceramide III, Cinnamonium Zeylanicum (Cinnamon Bark) Oil, Cymbopogon Nardus (Citronella) Oil, Ethoxydiglycol, Eugenia Caryophyllum (Clove Bud) Extract, Hippophae Rhamnoides (Sea Berry) Fruit and Seed Oils, Lavandula Angustifolia (Lavender) Oil, Limonene, Melaleuca Alternifolia (Tea Tree) Leaf Oil, Mentha piperita (Peppermint) Leaf Oil,

Olea Europaea (Olive Pomace) Oil, Oreganum Vulgare (Oregano) Leaf Oil, Pinene, Prunus Amygdalus Dulcis (Sweet Almond) Oil, Simmondsia Chinensis (Jojoba) Oil, Syzgium Aromaticum (Clove Bud) Oil, Thymol, Tocopherol Acetate, Trimethyl-Adipic Acid Copolymer.

PURPOSE

Antifungal

Uses

- proven clinically to cure most:
- athlete's foot (tinea pedis)
- ringworm (tinea corporis)

- Effectively soothes and relieves:
- itching
- burning
- cracking
- helps prevent most athlete's foot from coming back with daily use

Warnings

For external use only

Do not use on children under 2 years of age unless directed by a doctor

When using this product avoid contact with the eyes

Stop use and ask a doctor if

- there is no improvement within 4 weeks

Keep out of reach of children.

Get medical help or contact a Poison Control Center right away.

Do not use on children under 2 years of age unless directed by a doctor

When using this product, avoid contact with the eyes

Keep out of reach of children.

Get medical help or contact a Poison Control Center right away

Directions

clean the affected area and dry thoroughly

apply a thin layer over the affected area twice daily

supervise children in the use of this product

for athletes foot pay special attention to the spaces between toes

use daily for 4 weeks

FLAWLESS NAILS LABEL AND FLAWLESS NAILS BOX